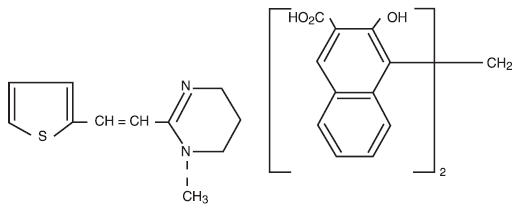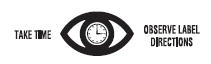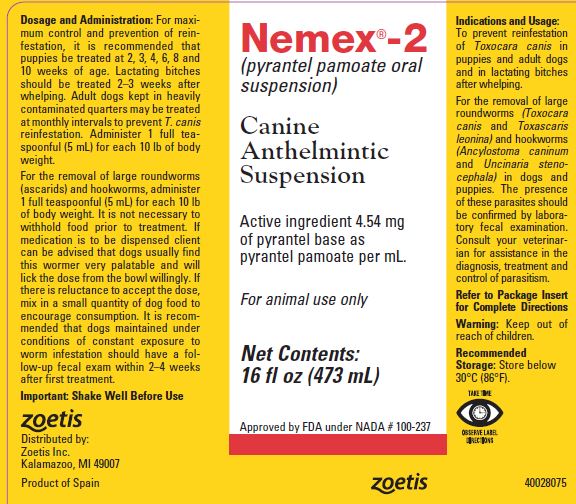 DRUG LABEL: Nemex 2
NDC: 54771-2934 | Form: SUSPENSION
Manufacturer: Zoetis Inc.
Category: animal | Type: OTC ANIMAL DRUG LABEL
Date: 20251023

ACTIVE INGREDIENTS: pyrantel pamoate 4.54 mg/1 mL

NEMEX®-2

NEMEX®-2
(pyrantel pamoate oral suspension)
CANINE ANTHELMINTIC SUSPENSION

FOR ANIMAL USE ONLY

DESCRIPTION

Nemex-2 is a suspension of pyrantel pamoate in a palatable caramel-flavored vehicle. Each mL contains 4.54 mg of pyrantel base as pyrantel pamoate.

Pyrantel pamoate is a compound belonging to a family classified chemically as tetrahydropyrimidines. It is a yellow, water-insoluble crystalline salt of the tetrahydropyrimidine base and pamoic acid containing 34.7% base activity. The chemical structure and name are given below:

(E)-1,4,5,6-Tetrahydro-1-methyl-2-[2-(2-thienyl) vinyl] pyrimidine 4,4' methylenebis [3-hydroxy-2-naphthoate] (1:1)

INDICATIONS AND USAGE

Nemex-2 suspension is a highly palatable formulation intended as a single treatment for the removal of large roundworms (Toxocara canis and Toxascaris leonina) and hookworms (Ancylostoma caninum and Uncinaria stenocephala) in dogs and puppies. The presence of these parasites should be confirmed by laboratory fecal exam. Consult your veterinarian for assistance in the diagnosis, treatment, and control of parasitism.

Nemex-2 suspension may also be used to prevent reinfestation of T. canis in puppies and adult dogs and in lactating bitches after whelping.

PRECAUTIONS

THIS PRODUCT IS A SUSPENSION AND AS SUCH WILL SEPARATE. TO INSURE UNIFORM RESUSPENSION AND TO ACHIEVE PROPER DOSAGE, IT IS EXTREMELY IMPORTANT THAT THE PRODUCT BE SHAKEN THOROUGHLY BEFORE EVERY USE.

KEEP OUT OF REACH OF CHILDREN

DOSAGE AND ADMINISTRATION

Administer 1 teaspoon (5 mL) for each 10 lb of body weight. It is not necessary to withhold food prior to or after treatment. Dogs usually find this dewormer very palatable and will lick the dose from the bowl willingly. If there is reluctance to accept the dose, mix in a small quantity of dog food to encourage consumption. It is recommended that dogs maintained under conditions of constant exposure to worm infestation should have a follow-up fecal exam within 2–4 weeks after treatment.

For maximum control and prevention of reinfestation, it is recommended that puppies be treated at 2, 3, 4, 6, 8, and 10 weeks of age. Lactating bitches should be treated 2–3 weeks after whelping. Adult dogs kept in heavily contaminated quarters may be treated at monthly intervals to prevent T. canis reinfestation.

SAFETY AND EFFICACY STUDIES

Critical (worm count) studies in dogs demonstrated that Nemex-2 at the recommended dosage is highly efficacious against T. leonina (99%), T. canis (85%), A. caninum (97%), and U. stenocephala (94%).
One of the most outstanding and significant features of Nemex-2 is its wide margin of therapeutic safety in dogs. The acute oral LD50 of pyrantel pamoate administered in gelatin capsules to female and male dogs is greater than 314 mg base per lb of body weight, which indicates a therapeutic index in excess of 138 times the recommended dosage. In subacute and chronic studies, no significant morphological abnormalities could be attributed to Nemex-2 when administered to dogs at daily dose rates up to 94 mg base per lb of body weight (40x) for periods of 19, 30, and 90 days. Clinical studies conducted in a wide variety of geographic locations using more than 40 different breeds of dogs showed no drug-induced toxic effects. Included in these studies were nursing pups, weaned pups, adults, pregnant bitches, and males at stud. Additional data have demonstrated the safe use of Nemex-2 in dogs having heartworm infestations and/or receiving medication for heartworms, dogs exposed to organophosphate flea collars or flea/tick dip treatments, and dogs undergoing concurrent treatment or medication at the time of worming such as immunization and antibacterial treatment.

RECOMMENDED STORAGE

Store below 30°C (86°F).

HOW SUPPLIED

Nemex-2 is supplied in 2 fl. oz. (60 mL) and 16 fl. oz. (473 mL) bottles.

Approved by FDA under NADA # 100-237

zoetis

Distributed by:
Zoetis Inc.
Kalamazoo, MI 49007

Revised: June 2019
40028076